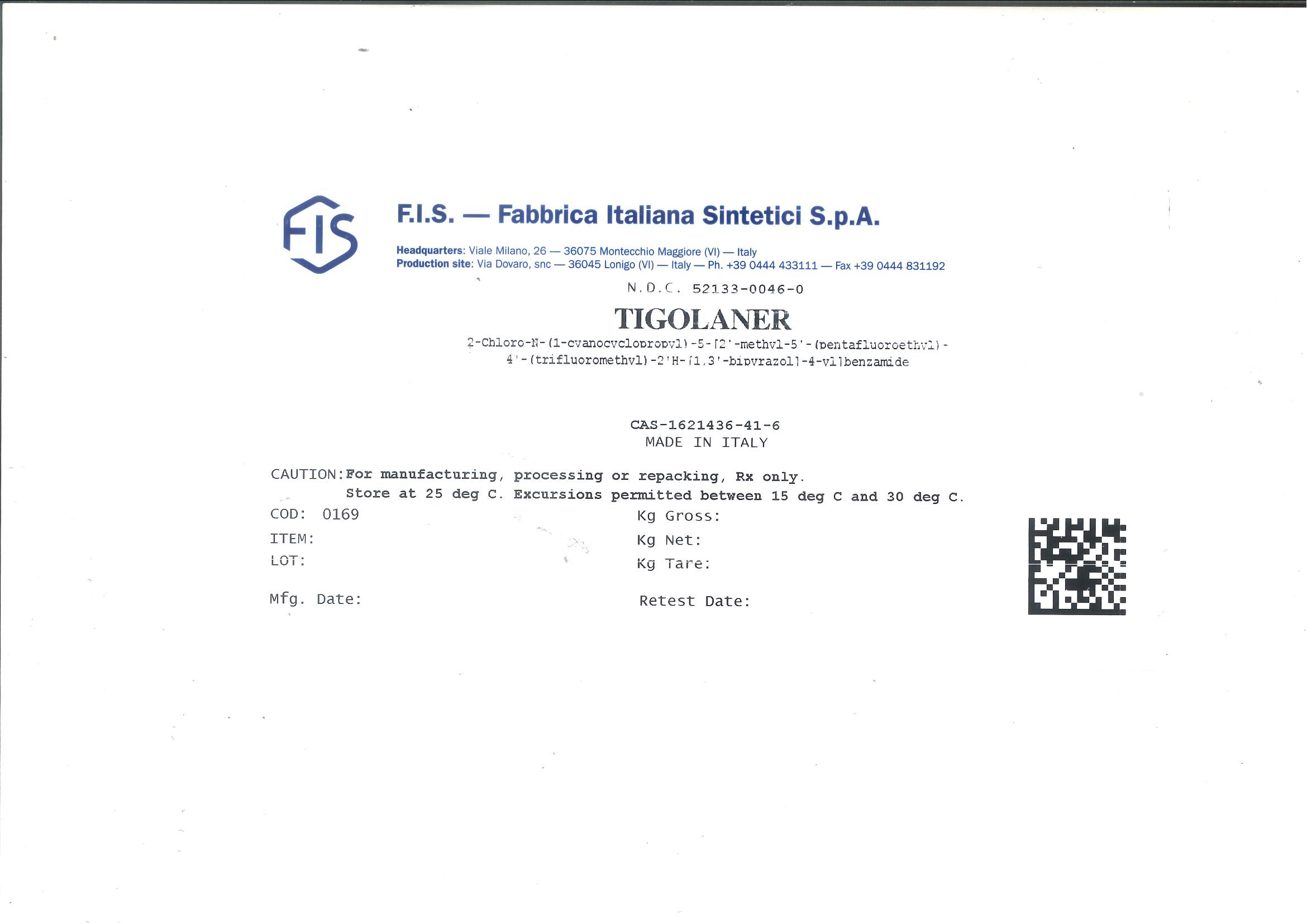 DRUG LABEL: TIGOLANER
NDC: 52133-0046 | Form: POWDER
Manufacturer: F.I.S. Fabbrica Italiana Sintetici  S.P.A.
Category: other | Type: BULK INGREDIENT - ANIMAL DRUG
Date: 20241120

ACTIVE INGREDIENTS: TIGOLANER 1 kg/1 kg

TIGOLANER